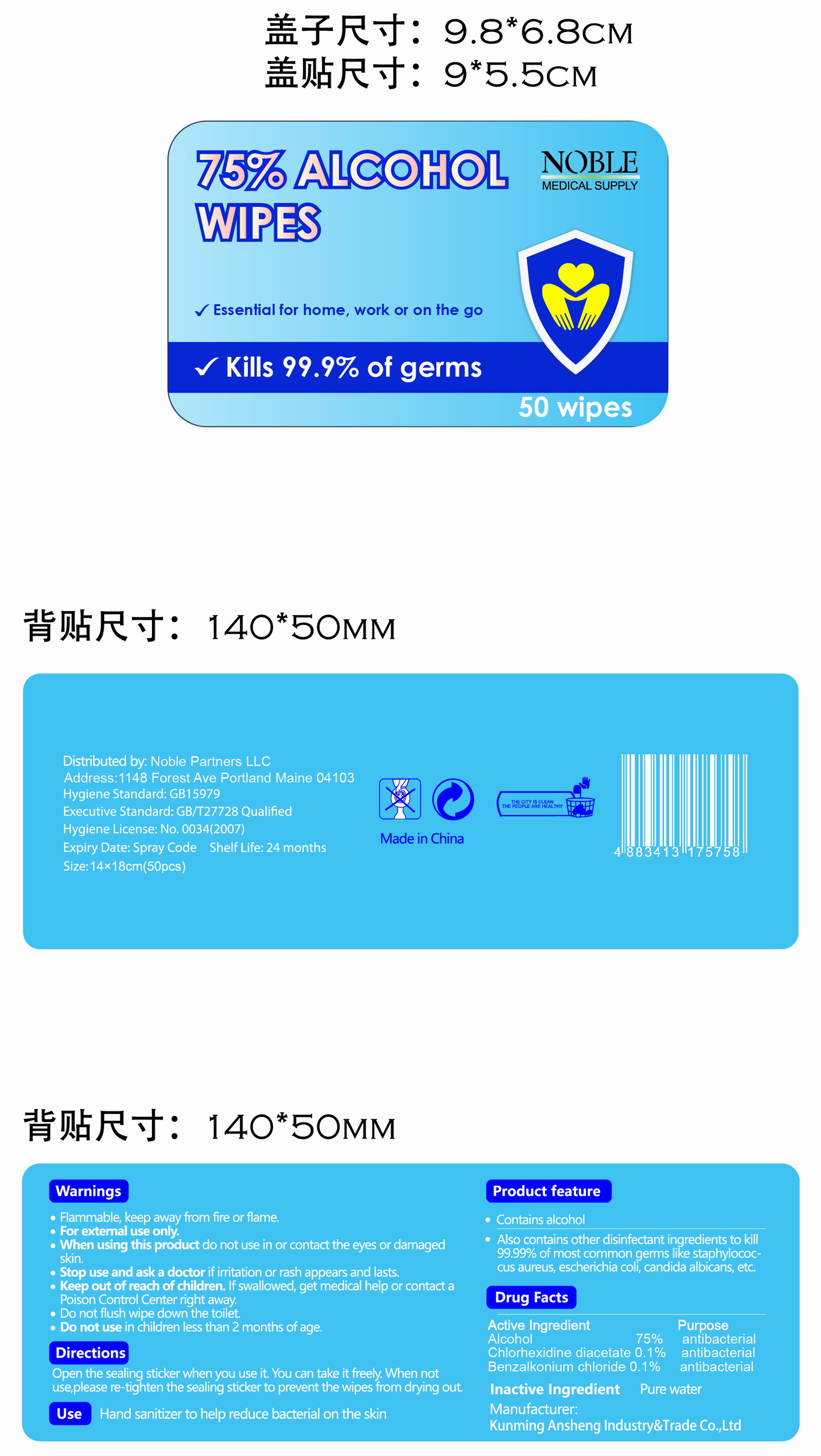 DRUG LABEL: Noble 75% Alcohol Wipes
NDC: 78183-021 | Form: CLOTH
Manufacturer: Kunming Ansheng Industry & Trade Co., Ltd.
Category: otc | Type: HUMAN OTC DRUG LABEL
Date: 20201231

ACTIVE INGREDIENTS: CHLORHEXIDINE ACETATE 0.001 U/1 U; BENZALKONIUM CHLORIDE 0.001 U/1 U; ALCOHOL 0.75 U/1 U
INACTIVE INGREDIENTS: WATER

NOBLE 75% Alcohol Wipes

Active Ingredient(s)

Alcohol 75% v/v.
Chlorhexidine diacetate 0.1% v/v.
Benzalkonium chloride 0.1% v/v.

Purpose

Antibacterial; kill 99.99% of most common germs.

Use

Hand sanitizer to help reduce bacterial on the skin.

Warnings

For external use only. Flammable. Keep away from heat or flame

Do not use

- in children less than 2 months of age
- on open skin wounds

When using this product do not use in or contact the eyes or damaged skin.

Stop use and ask a doctor if irritation or rash appears and lasts.

Keep out of reach of children. If swallowed, get medical help or contact a Poison Control Center right away.

Directions

- Open the sealing sticker when you use it.
- You can take it freely.
- When not use, please re-tighten the sealing sticker to prevent the wipes from drying out.

Inactive ingredients

Pure water

Package Label - Principal Display Panel

50 CLOTH in 1 BAG

NDC: 78183-019-01